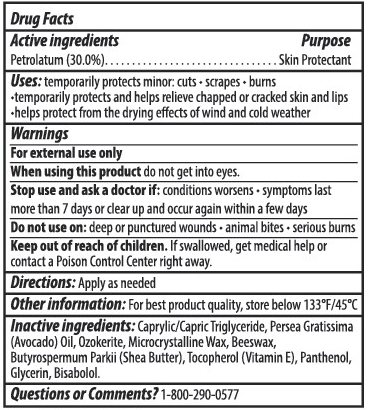 DRUG LABEL: Healing Balm Skin Protectant
NDC: 63645-185 | Form: STICK
Manufacturer: OraLabs
Category: otc | Type: HUMAN OTC DRUG LABEL
Date: 20251201

ACTIVE INGREDIENTS: PETROLATUM 30 mg/1 g
INACTIVE INGREDIENTS: WHITE WAX 10 mg/1 g; MICROCRYSTALLINE WAX 7 mg/1 g

Drug Facts

Active ingredient

Petrolatum, 30%

Purpose

Skin Protectant

Keep Out of Reach of Children

If swallowed get medical help or contact a Poison Control Center right away.

Uses

temporarily protects minor: cuts· scrapes· burns. Temporarily protects and helps relieve chapped or cracked skin and lips· helps protect from the drying effects of wind and cold weather.

Warnings

For external use only. When using this product do not get into eyes. Stop use and ask a doctor if ·conditions worsens· symptoms last more than 7 days or clear up and occur again within a few days. Do not use on· deep or punctured wounds· animal bites ·serious burns

Directions

Apply as needed.

Inactive Ingredients

Caprylic/Capric Triglyceride, Persea Gratissima (Avocado) Oil, Ozokerite, Microcrystalline Wax, Beeswax, Butyrospermum Parkii (Shea Butter), Tocopherol (Vitamin E), Panthenol, Glycerin, Bisabolol.

Questions

1-800-290-0577